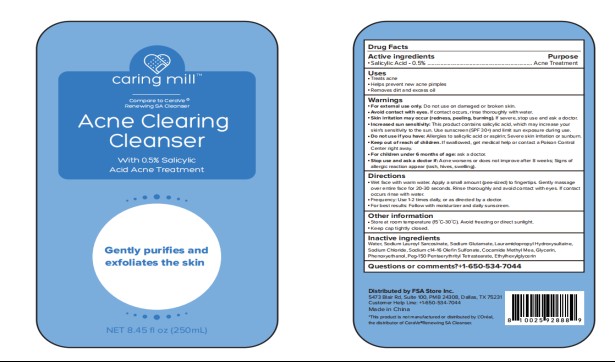 DRUG LABEL: Caring Mill Acne Clearing Cleanser
NDC: 81522-100 | Form: LIQUID
Manufacturer: FSA Store Inc. (Caring Mills)
Category: otc | Type: HUMAN OTC DRUG LABEL
Date: 20251002

ACTIVE INGREDIENTS: SALICYLIC ACID 0.5 g/100 mL
INACTIVE INGREDIENTS: COCAMIDE METHYL MEA; LAURAMIDOPROPYL HYDROXYSULTAINE; SODIUM C14-16 OLEFIN SULFONATE; GLYCERIN; SODIUM GLUTAMATE; ETHYLHEXYLGLYCERIN; SODIUM LAUROYL SARCOSINATE; SODIUM CHLORIDE; WATER; PHENOXYETHANOL; PEG-150 PENTAERYTHRITYL TETRASTEARATE

81522-100-01Caring Mill Acne Clearing Cleanser

ACTIVE INGREDIENT

SALICYLIC ACID： 0.5%

INACTIVE INGREDIENT

WATER
SODIUM LAUROYL SARCOSINATE
SODIUM GLUTAMATE
LAURAMIDOPROPYL HYDROXYSULTAINE
SODIUM CHLORIDE
SODIUM C14-16 OLEFIN SULFONATE
COCAMIDE METHYL MEA
GLYCERIN
SODIUM CHLORIDE
PHENOXYETHANOL
PEG-150 PENTAERYTHRITYL TETRASTEARATE
ETHYLHEXYLGLYCERIN

PURPOSE

Acne Medication

Keep out of reach of children

WARNINGS

For external use only.

When using this product

Skin irritation and dryness is more likely to occur if you use another topical acne medication at the same time. If irritation occurs, only use one topical acne medication at a time.

When using this product

If swallowed, get medical help or contact a Poison Control Center right away.

DOSAGE AND ADMINISTRATION

Wet the skin and gently massage for 1-2 minutes and rinse well.
If bothersome dryness or peeling occurs, reduce frequency of use.

INDICATIONS AND USAGE

Dispense a small amount into hand and mix with a little water.
Apply a thin layer over the entire affected area in a circular motion and rinse thoroughly with warm water two times daily.
Because excessive dry of the skin may occur, start with one application daily, then gradually increase to two times daily if needed or as directed by a doctor.
If bothersome dryness or peeling occurs, reduce application to once a day or every other day.